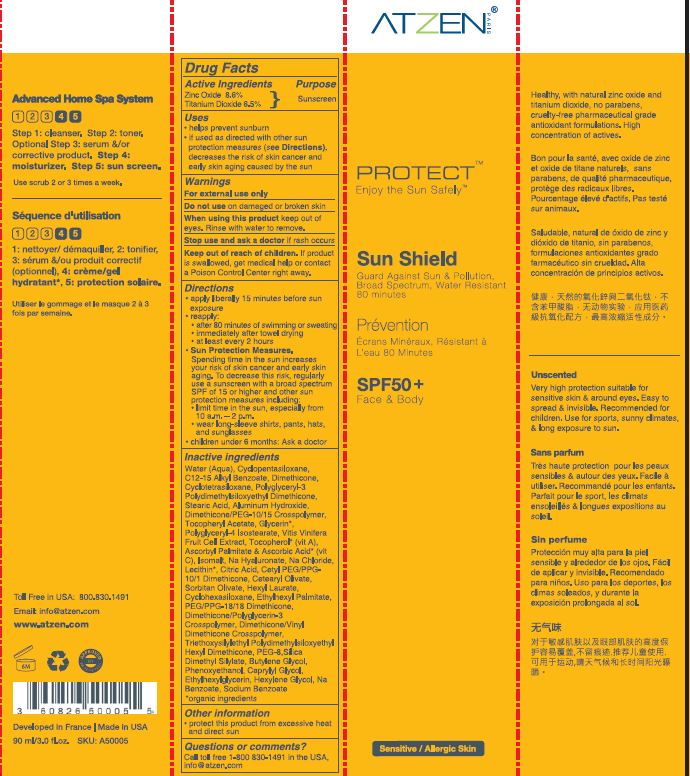 DRUG LABEL: Sun Shield SPF 50
NDC: 62742-4161 | Form: CREAM
Manufacturer: ALLURE LABS INC
Category: otc | Type: HUMAN OTC DRUG LABEL
Date: 20171215

ACTIVE INGREDIENTS: ZINC OXIDE 86 mg/1 mL; TITANIUM DIOXIDE 65 mg/1 mL
INACTIVE INGREDIENTS: WATER; ALKYL (C12-15) BENZOATE; DIMETHICONE; POLYGLYCERYL-3 POLYDIMETHYLSILOXYETHYL DIMETHICONE (4000 MPA.S); ALUMINUM HYDROXIDE; STEARIC ACID; GLYCERIN; SODIUM CHLORIDE; POLYGLYCERYL-4 ISOSTEARATE; CETYL PEG/PPG-10/1 DIMETHICONE (HLB 2); VITIS VINIFERA FRUIT RIND; HEXYL LAURATE; CETEARYL OLIVATE; SORBITAN OLIVATE; TOCOPHEROL; .ALPHA.-TOCOPHEROL ACETATE; SODIUM CHONDROITIN SULFATE (PORCINE; 5500 MW); PEG/PPG-18/18 DIMETHICONE; DIMETHICONE/VINYL DIMETHICONE CROSSPOLYMER (SOFT PARTICLE); ETHYLHEXYL PALMITATE; SILICA DIMETHYL SILYLATE; BUTYLENE GLYCOL; HYALURONATE SODIUM; PHENOXYETHANOL; CAPRYLYL GLYCOL; ETHYLHEXYLGLYCERIN; HEXYLENE GLYCOL; ASCORBIC ACID; ASCORBYL PALMITATE; CITRIC ACID MONOHYDRATE; LECITHIN, SOYBEAN; TRIEPOXYCYCLOHEXASILANE; SODIUM BENZOATE

Drug Facts

Active Ingredients:

Zinc Oxide - 8.6%

Titanium Dioxide - 6.5%

Purpose: Sunscreen

INDICATIONS AND USAGE

Uses: Helps prevent sunburn. If used as directed with other sun protection measures (see Direction), decreases the risk of skin cancer and early skin aging caused by the sun.

WARNINGS

For external use only.

Do not use on damaged or broken skin.

WHEN USING

Keep out of eyes. Rinse with water to remove.

Stop use and ask a doctor if rash occurs.

KEEP OUT OF REACH OF CHILDREN

If product is swallowed, get medical help or contact a Poison Control Center right away.

Directions:

- Apply liberally 15 minutes prior to sun exposure.
- Reapply: after 80 minutes of swimming or sweating. Immediately after towel drying. At least every 2 hours.
- Sun Protection Measures. Spending time in the sun increases your risk of skin cancer and early skin aging. To decrease the risk, regularly use a sunscreen with a broad spectrum SPF of 15 or higher and other sun protection measures including:
- limit time in sun sun, especially from 10 am - 2 pm.
- wear long-sleeve shirts, pants, hats and sunglasses.
- Children under 6 months: Ask a doctor.

INACTIVE INGREDIENT

Water (Aqua), Cyclopenatasiloxane, C12-15 Alkyl Benzoate, Dimethicone, Cyclotetrasiloxane, Polyglyceryl-3 Polydimethylsiloxyethyl Dimethicone, Alminum Hydroxide, Stearic Acid, Dimethicone/PEG-10/15 Crosspolymer, Glycerin, Sodium Chloride, Polyglyceryl-4 Isostearate, Vitis Vinifera, Cetyl PEG/PPG-10/1 Dimethicone, Hexyl Laurate, Cetearyl Olivate, Sorbitan Olivate, Cyclohexasiloxane, Tocopherol, Tocopheryl Acetate, PEG/PPG-18/18 Dimethicone, Dimethicone/Polyglycerin-3 Crosspolymer, Isomalt, Dimethicone / Vinyl Dimethicone Crosspolymer Triethoxysilylethyl Polydimethylsiloxyethyl Hexyl Dimethicone, Ethylhexyl Palmitate, Silica Dimethyl Silylate, Butylene Glycol, Sodium Hyaluronate, Phenoxyethanol, Caprylyl Glycol, Ethylhexylglycerin, Hexylene Glycol, PEG-8, Ascorbic Acid, Ascorbyl Palmitate, Citric Acid, Sodium Benzoate.

OTHER SAFETY INFORMATION

Protect this product from excessive heat and direct sun.

QUESTIONS

Call toll free 1-800 830-1491 in the USA.

info@atzen.com

PACKAGE LABEL

Toll free in USA: 800.830.1491

Email: info@atzen.com

www.atzen.com

Developed in France. Made in USA.